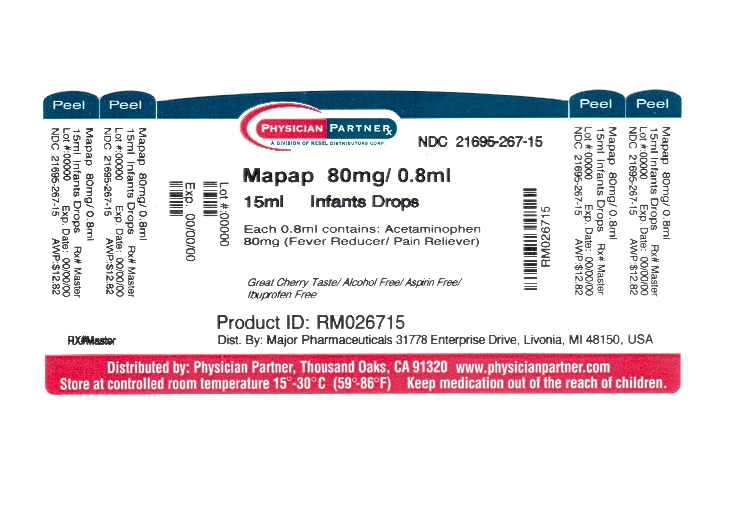 DRUG LABEL: mapap
NDC: 21695-267 | Form: SUSPENSION/ DROPS
Manufacturer: Rebel Distributors Corp
Category: otc | Type: HUMAN OTC DRUG LABEL
Date: 20120117

ACTIVE INGREDIENTS: ACETAMINOPHEN 80 mg/0.8 mL
INACTIVE INGREDIENTS: ANHYDROUS CITRIC ACID; BUTYLPARABEN; CARBOXYMETHYLCELLULOSE SODIUM; CARRAGEENAN; FD&C RED NO. 40; GLYCERIN; HIGH FRUCTOSE CORN SYRUP; HYDROXYETHYL CELLULOSE (100 MPA.S AT 2%); CELLULOSE, MICROCRYSTALLINE; PROPYLENE GLYCOL; WATER; SODIUM BENZOATE; SORBITOL

Major Pharmaceuticals Infants' Mapap® Concentrated Drops Drug Facts

Active ingredient (in each 0.8 mL)

Acetaminophen 80 mg

Purpose

Fever reducer/pain reliever

Uses

temporarily:

- reduces fever
- relieves minor aches and pains due to:
- the common cold
- flu
- headache
- sore throat
- toothache

Warnings

Liver warning: This product contains acetaminophen. Severe liver damage may occur if your child takes

- more than 5 doses in 24 hours, which is the maximum daily amount
- with other drugs containing acetaminophen

Sore throat warning: If sore throat is severe, persists for more than 2 days, is accompanied or followed by fever, headache, rash, nausea, or vomiting, consult a doctor promptly.

Do not use

with any other drug containing acetaminophen (prescription or nonprescription). If you are not sure whether a drug contains acetaminophen, ask a doctor or pharmacist.

Ask a doctor before use if your child has

liver disease

Ask a doctor or pharmacist before use if your child is

taking the blood thinning drug warfarin

Stop use and ask a doctor if

- pain gets worse or lasts more than 5 days
- fever gets worse or lasts more than 3 days
- new symptoms occur
- redness or swelling is present

These could be signs of a serious condition.

Keep out of reach of children.

In case of overdose, get medical help or contact a Poison Control Center right away. (1-800-222-1222) Quick medical attention is critical even if you do not notice any signs or symptoms.

Directions

- do not give more than directed (see Liver warning)
- shake well before using
- find right dose on chart. If possible, use weight to dose; otherwise use age.
- use only enclosed dropper designed for use with this product. Do not use any other dosing device.
- fill to dose level
- dispense liquid slowly into child’s mouth, toward inner cheek
- if needed, repeat dose every 4 hours while symptoms last
- do not give more than 5 times in 24 hours
- do not give for more than 5 days unless directed by a doctor
- replace dropper tightly to maintain child resistance
- this product does not contain directions or complete warnings for adult use

Dosing Chart
Weight(lb) | Age(yr) | Dose (mL)
under 24 | under 2 years | ask a doctor
24-35 | 2–3 years | 1.6 mL (0.8 + 0.8 mL)

Attention: use only enclosed dropper specifically designed for use with this product. Do not use any other dosing device.

Other information

- store at 20°-25°C (68°-77°F)
- do not use if printed bottle wrap is broken or missing

Inactive ingredients

anhydrous citric acid, butylparaben, carboxymethylcellulose sodium, carrageenan, FD&C red no. 40, flavor, glycerin, high fructose corn syrup, hydroxyethyl cellulose, microcrystalline cellulose, propylene glycol, purified water, sodium benzoate, sorbitol solution

Questions or comments?

1-800-616-2471